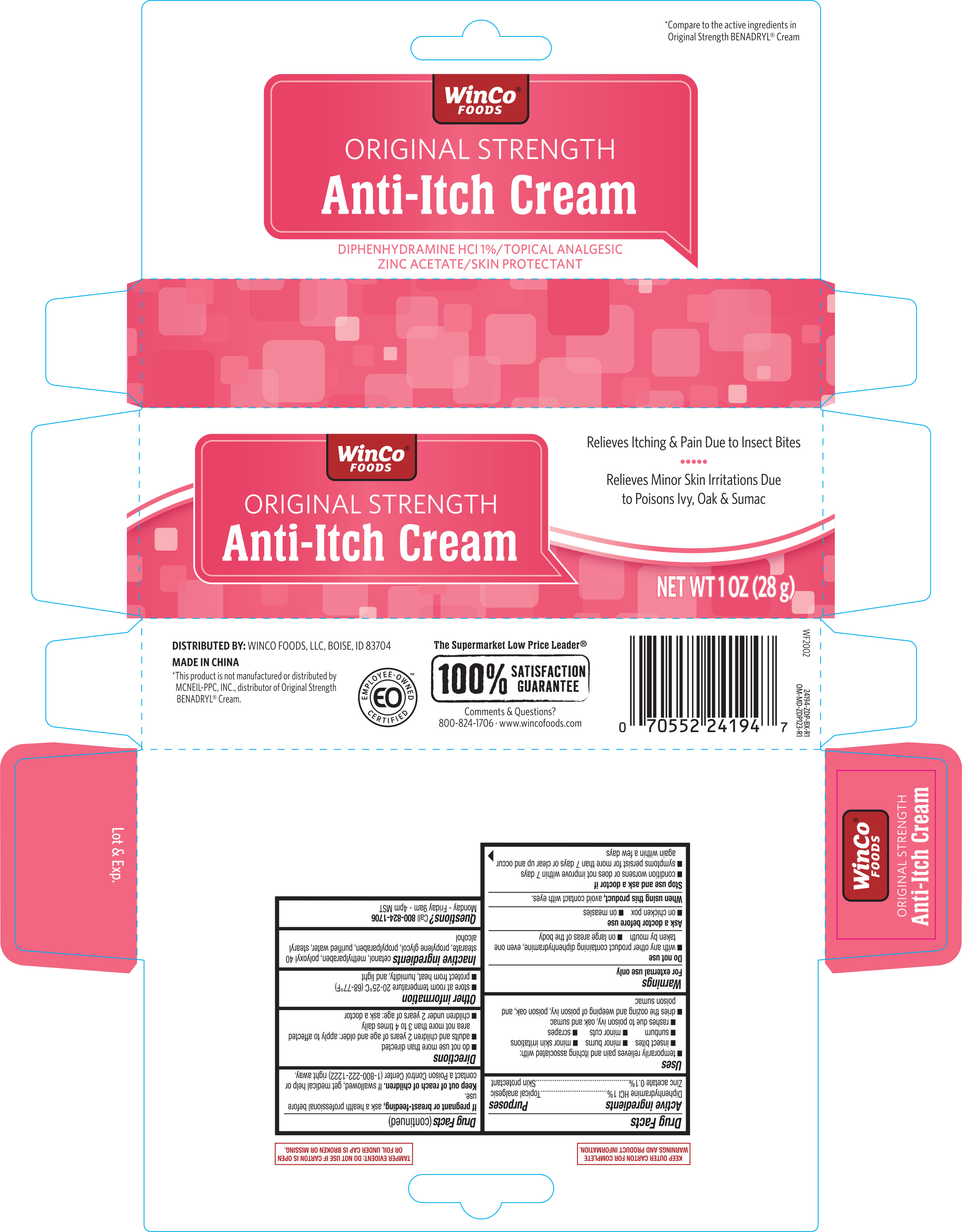 DRUG LABEL: WinCo Original Strength Anti-Itch
NDC: 67091-277 | Form: CREAM
Manufacturer: WinCo Foods, LLC
Category: otc | Type: HUMAN OTC DRUG LABEL
Date: 20251024

ACTIVE INGREDIENTS: DIPHENHYDRAMINE HYDROCHLORIDE 10 mg/1 g; ZINC ACETATE 1 mg/1 g
INACTIVE INGREDIENTS: PROPYLPARABEN; CETYL ALCOHOL; WATER; METHYLPARABEN; POLYOXYL 40 STEARATE; PROPYLENE GLYCOL; STEARYL ALCOHOL

Winco Original Strength Anti Itch Cream 1 oz 24194 ZDP

ACTIVE INGREDIENT

Active ingredients.............................................................................Purposes

Diphenhydramine HCl 1%...................................................... Topical analgesic

Zinc acetate 0.1%...................................................................... Skin protectant

Uses

temporarily relieves pain and itching associated with:

- insect bites
- minor burns
- minor skin irritations
- sunburn
- minor cuts
- scrapes
- rashes due to poison ivy, oak, and sumac

dries the oozing and weeping of poison ivy, poison oak, and poison sumac

Warnings

For external use only

Do not use

- with any other product containing diphenhydramine, even one taken by mouth
- on large areas of the body

Ask a doctor before use

- on chicken pox
- on measles

When using this product, avoid contact with eyes.

Stop use and ask a doctor if

- condition worsens or does not improve within 7 days
- symptoms persist for more than 7 days or clear up and occur again within a few days

PREGNANCY OR BREAST FEEDING

If pregnant or breast-feeding, ask a health professional before use.

Keep out of reach of children. If swallowed, get medical help or contact a Poison Control Center (1-800-222-1222) right away.

Directions

- do not use more than directed
- adults and children 2 years of age and older: apply to affected area not more than 3 to 4 times daily
- children under 2 years of age: ask a doctor

Other information

- store at room temperature 20-25°C (68-77°F)
- protect from heat, humidity, and light

INACTIVE INGREDIENT

Inactive ingredients cetanol, methylparaben, polyoxyl 40 stearate, propylene glycol, propylparaben, purified water, stearyl alcohol

DOSAGE AND ADMINISTRATION

DISTRIBUTED BY:

WINCO FOODS, LLC

BOISE, ID 83704

MADE IN CHINA